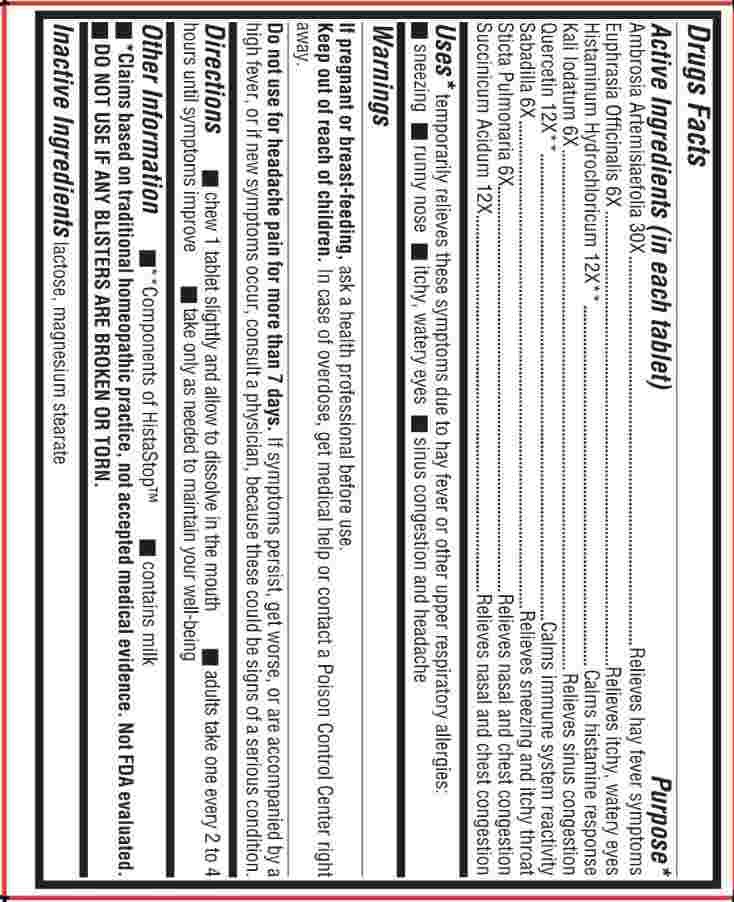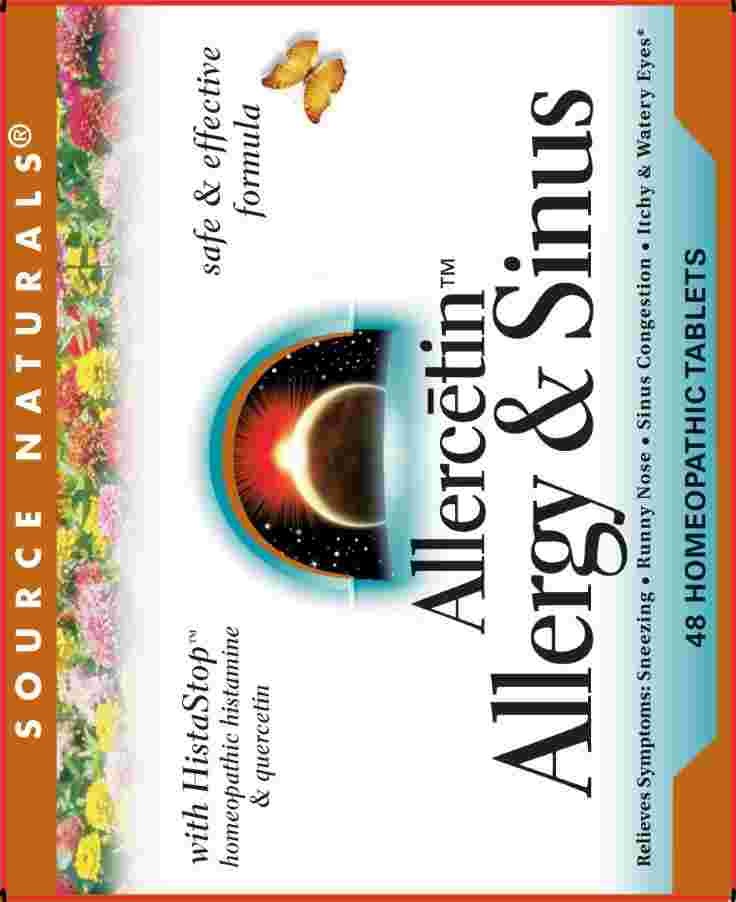 DRUG LABEL: Allercetin
NDC: 64471-196 | Form: TABLET, CHEWABLE
Manufacturer: Source Naturals, Inc.
Category: homeopathic | Type: HUMAN OTC DRUG LABEL
Date: 20241031

ACTIVE INGREDIENTS: EUPHRASIA STRICTA 6 [hp_X]/1 mg; POTASSIUM IODIDE 6 [hp_X]/1 mg; SCHOENOCAULON OFFICINALE SEED 6 [hp_X]/1 mg; LOBARIA PULMONARIA 6 [hp_X]/1 mg; HISTAMINE DIHYDROCHLORIDE 12 [hp_X]/1 mg; QUERCETIN 12 [hp_X]/1 mg; SUCCINIC ACID 12 [hp_X]/1 mg; AMBROSIA ARTEMISIIFOLIA WHOLE 30 [hp_X]/1 mg
INACTIVE INGREDIENTS: LACTOSE; MAGNESIUM STEARATE

DRUG FACTS:

ACTIVE INGREDIENTS:

(in each tablet) Ambrosia Artemisiaefolia 30X, Euphrasia Officinalis 6X, Histaminum Hydrochloricum 12X,** Kali Iodatum 6X, Quercetin 12X,** Sabadilla 6X, Sticta Pulmonaria 6X, Succinicum Acidum 12X.

**Components of HistaStop

PURPOSE:

*Ambrosia Artemisiaefolia – Relieves hay fever symptoms, Euphrasia Officinalis – Relieves itchy, watery eyes, Histaminum Hydrochloricum – Calms histamine response, Kali Iodatum – Relieves sinus congestion, Quercetin – Calms immune system reactivity, Sabadilla – Relieves sneezing and itchy throat, Sticta Pulmonaria – Relieves nasal and chest congestion, Succinicum Acidum – Relieves nasal and chest congestion

*Claims based on traditional homeopathic practice, not accepted medical evidence. Not FDA evaluated.

USES:

*temporary relieves these symptoms due to hay fever or other upper respiratory allergies:

• sneezing • runny nose • itchy and watery eyes • sinus congestion and headache.

*Claims based on traditional homeopathic practice, not accepted medical evidence. Not FDA evaluated.

WARNINGS:

If pregnant or breast-feeding, ask a health professional before use.

Keep out of reach of children. In case of overdose, get medical help or contact a Poison Control Center right away.

Do not use for headache pain for more than 7 days. If symptoms persist, get worse, or are accompanied by a high fever, or if new symptoms occur, consult a physician, because these could be signs of a serious condition.

Tamper Evident: Do not use if foil blister backing is broken. Foil backing is printed with product name and lot number.

DO NOT USE IF ANY BLISTERS ARE BROKEN OR TORN.

Contains milk

KEEP OUT OF REACH OF CHILDREN:

In case of overdose, get medical help or contact a Poison Control Center right away.

DIRECTIONS:

• chew 1 tablet slightly and allow to dissolve in the mouth.

• adults take one every 2 to 4 hours until symptoms improve.

• take only as needed to maintain your well-being.

INACTIVE INGREDIENTS:

lactose, magnesium stearate

QUESTIONS:

Distributed by:

Source Naturals, Inc.

P.O. Box 2118. Santa Cruz, CA. USA 95062

www.sourcenaturals.com

PACKAGE LABEL DISPLAY:

SOURCE NATURALS

with HistaStop safe & effective

homeopathic histamine formula

& quercetin

Allercetin

Allergy & Sinus

Relieves Symptoms: Sneezing • Runny Nose • Sinus Congestion • Itchy & Watery Eyes

48 HOMEOPATHIC TABLETS